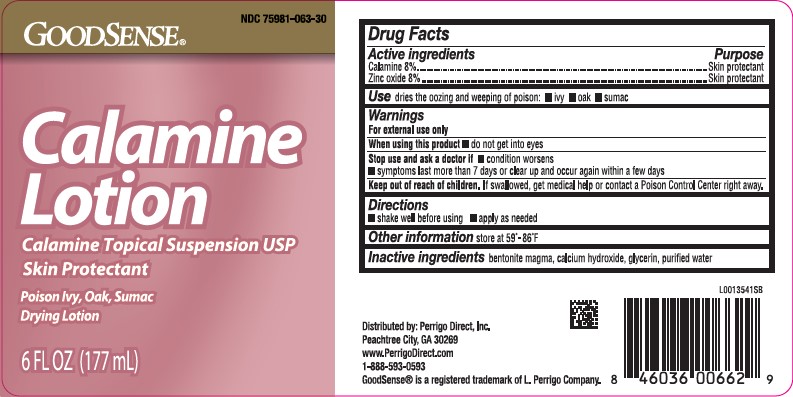 DRUG LABEL: Calamine
NDC: 75981-063 | Form: LOTION
Manufacturer: Perrigo Direct, Inc 
Category: otc | Type: HUMAN OTC DRUG LABEL
Date: 20260219

ACTIVE INGREDIENTS: FERRIC OXIDE RED 8 mg/1 mL; ZINC OXIDE 8 mg/1 mL
INACTIVE INGREDIENTS: BENTONITE; CALCIUM HYDROXIDE; GLYCERIN; WATER

Good Sense 063.001/063AA
Calamine Lotion

Active ingredients

Calamine 8%
Zinc oxide 8%

Purpose

Skin protectant

Use

dries the oozing and weeping of poison:

- ivy
- oak
- sumac

Warnings

For external use only

When using this product

- do not get into eyes

Stop use and ask a doctor if

- condition worsens
- symptoms last more than 7 days or clear up and occur again within a few days

Keep out of reach of children.

If swallowed, get medical help or contact a Poison Control Center right away.

Directions

- shake well before using
- apply as needed

Other information

store at 59⁰ - 86⁰F

Inactive ingredients

bentonite magma, calcium hydroxide, glycerin, purified water

ADVERSE REACTION

Distributed by: Perrigo Direct, Inc.

Peachtree City, GA 30269

www.PerrigoDirect.com

1-888-593-0593

GoodSense® is a registered trademark of L. Perrigo Company.

Principal Panel Display

GOODSENSE®

NDC 75981-063-30

Calamine Lotion

Calamine Topical Suspension USP

Skin Protectant

Poison Ivy, Oak, Sumac

Drying Lotion

6 FL OZ (177 mL)